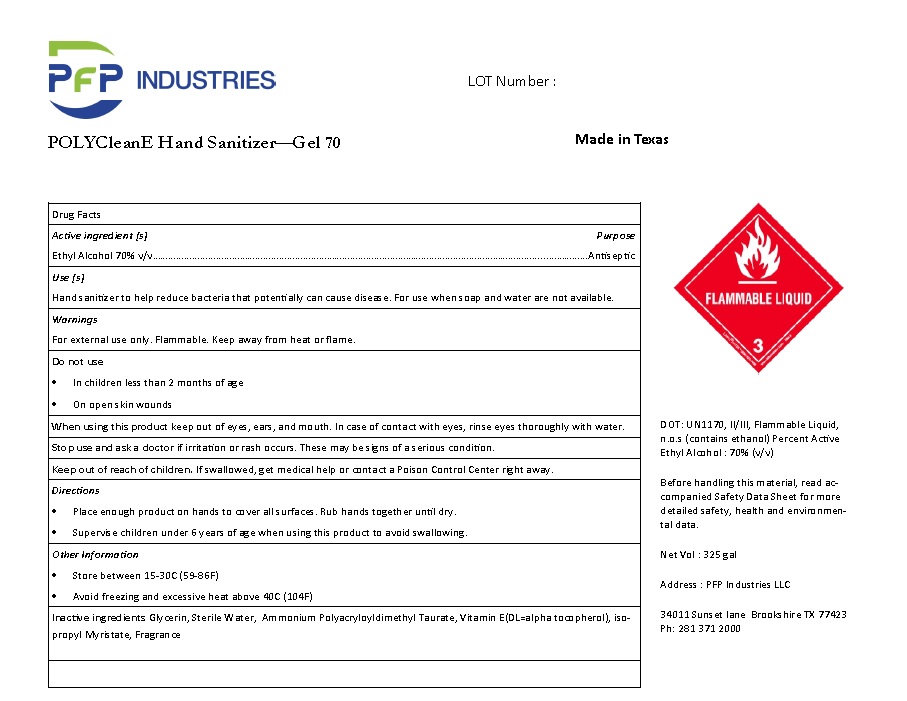 DRUG LABEL: PFP POLYcleanE Hand Sanitizer - Gel 70
NDC: 77034-009 | Form: GEL
Manufacturer: Pfp Industries, LLC (a Global Enterprise)
Category: otc | Type: HUMAN OTC DRUG LABEL
Date: 20210113

ACTIVE INGREDIENTS: ALCOHOL 70 L/100 L
INACTIVE INGREDIENTS: GLYCERIN; WATER; AMMONIUM POLYACRYLOYLDIMETHYL TAURATE (55000 MPA.S); .ALPHA.-TOCOPHEROL; ISOPROPYL MYRISTATE

PFP POLYcleanE Hand Sanitizer - Gel 70

Drug Facts

Active ingredient [s]
Ethyl Alcohol 70% v/v

Purpose
Antiseptic

INDICATIONS AND USAGE

Use [s]
Hand sanitizer to help reduce bacteria that potentially can cause disease. For use when soap and water are not available.

Warnings
For external use only. Flammable. Keep away from heat or flame.

Do not use
•In children less than 2 months of age
•On open skin wounds

When using this product keep out of eyes, ears, and mouth. In case of contact with eyes, rinse eyes thoroughly with water.

Stop use and ask a doctor if irritation or rash occurs. These may be signs of a serious condition.

Keep out of reach of children. If swallowed, get medical help or contact a Poison Control Center right away.

Directions
•Place enough product on hands to cover all surfaces. Rub hands together until dry.
•Supervise children under 6 years of age when using this product to avoid swallowing.

Other Information
•Store between 15-30C (59-86F)
•Avoid freezing and excessive heat above 40C (104F)

INACTIVE INGREDIENT

Inactive ingredients Glycerin, Sterile Water, Ammonium Polyacryloyldimethyl Taurate, Vitamin E(DL=alpha tocopherol), iso-propyl Myristate, Fragrance

Product Labeling

PfP INDUSTRIES LOT Number :

POLYCleanE Hand Sanitizer—GEL 70 MADE IN TEXAS

FLAMMABLE LIQUID

3

DOT: UN1170, II/III, Flammable Liquid,
n.o.s (contains ethanol) Percent Active
Ethyl Alcohol : 70% (v/v)

Before handling this material, read ac-
companied Safety Data Sheet for more
detailed safety, health and environmen-
tal data.

Net Vol : 325 gal

Address : PFP Industries LLC

34011 Sunset lane Brookshire TX 77423
Ph: 281 371 2000

res 8.22.20